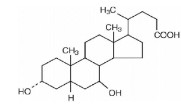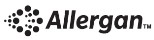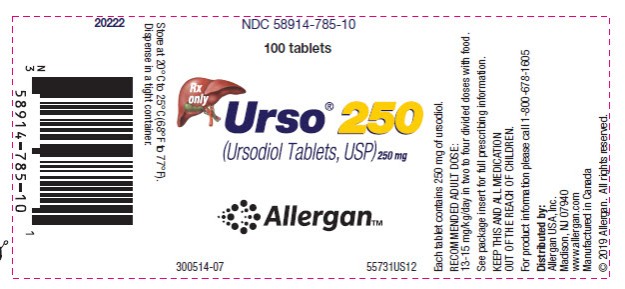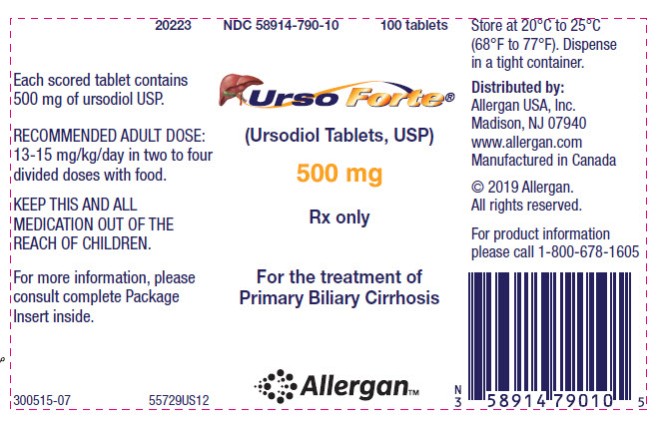 DRUG LABEL: Urso 250
NDC: 58914-785 | Form: TABLET, FILM COATED
Manufacturer: Allergan, Inc.
Category: prescription | Type: HUMAN PRESCRIPTION DRUG LABEL
Date: 20230112

ACTIVE INGREDIENTS: Ursodiol 250 mg/1 1
INACTIVE INGREDIENTS: MICROCRYSTALLINE CELLULOSE; POVIDONE, UNSPECIFIED; Polyethylene glycol 3350; Magnesium stearate; HYPROMELLOSE, UNSPECIFIED; ETHYLCELLULOSE, UNSPECIFIED; Dibutyl sebacate; Polyethylene glycol 8000; Carnauba wax; SODIUM STARCH GLYCOLATE TYPE A; CETYL ALCOHOL; SODIUM LAURYL SULFATE; HYDROGEN PEROXIDE

HIGHLIGHTS OF PRESCRIBING INFORMATION

These highlights do not include all the information needed to use URSO 250 and URSO FORTE safely and effectively. See full prescribing information for URSO 250 and URSO FORTE.
URSO 250® (ursodiol) tablets, for oral use
URSO FORTE® (ursodiol) tablets, for oral use
Initial U.S. Approval: 1997

RECENT MAJOR CHANGES

Warnings and Precautions (5.2) 1/2023

1 INDICATIONS AND USAGE

URSO 250 and URSO Forte (ursodiol) tablets are bile acids indicated for the treatment of patients with primary biliary cholangitis. (1)

2 DOSAGE AND ADMINISTRATION

- Recommended adult dosage: 13-15 mg/kg/day administered in two to four divided doses with food. (2.1)
- Scored URSO Forte tablet: scored tablet can be broken in halves to provide recommended dosage. (2.3, 16)

3 DOSAGE FORMS AND STRENGTHS

- URSO 250: 250 mg tablet (3)
- URSO Forte: 500 mg scored tablet (3)

4 CONTRAINDICATIONS

Patients with complete biliary obstruction and known hypersensitivity or intolerance to ursodiol or any of the components of the formulation. (4)

5 WARNINGS AND PRECAUTIONS

- Abnormal Liver Function Tests: Liver function tests (γ-GT, alkaline phosphatase, AST, ALT) and bilirubin level should be monitored. Treatment discontinuation should be considered if parameters increase to a level considered clinically significant in patients with stable historical liver function test levels. Caution should be exercised to maintain patients’ bile flow. (5.1)
- Enteroliths in Patients with Risk for Intestinal Stenosis or Stasis:

Monitor for obstructive gastrointestinal symptoms; if symptoms occur, hold ursodiol until a clinical evaluation has been conducted. (5.2)

6 ADVERSE REACTIONS

Most common adverse reactions reported with the use of ursodiol during worldwide postmarketing and clinical experience (≥1%) are, in alphabetical order: abdominal discomfort, abdominal pain, alopecia, diarrhea, nausea, pruritus, and rash. (6)

To report SUSPECTED ADVERSE REACTIONS, contact Allergan at 1-800-678-1605 or FDA at 1-800-FDA-1088 or www.fda.gov/medwatch.

7 DRUG INTERACTIONS

- Bile Acid Sequestering Agents: May interfere with the action of URSO 250 and URSO Forte by reducing its absorption. (7.1)
- Aluminum-based Antacids: May interfere with the action of URSO 250 and URSO Forte by reducing its absorption. (7.2)
- Drugs that alter the metabolism of lipids or induce cholestasis may interfere with the action of URSO 250 and URSO Forte. (7.3)

FULL PRESCRIBING INFORMATION

1 INDICATIONS AND USAGE

URSO 250 and URSO Forte (ursodiol) tablets are indicated for the treatment of patients with primary biliary cholangitis (PBC).

2 DOSAGE AND ADMINISTRATION

2.1 General Dosing Information

The recommended adult dosage for URSO 250 and URSO Forte in the treatment of PBC is 13-15 mg/kg/day administered in two to four divided doses with food. Dosing regimen should be adjusted according to each patient’s need at the discretion of the physician.

2.2 Liver Function Tests

Liver function tests (γ-GT, alkaline phosphatase, AST, ALT) and bilirubin levels should be monitored every month for three months after start of therapy, and every six months thereafter [see Warnings and Precautions (5.1)].

2.3 Scoring the URSO Forte Tablet

The URSO Forte scored tablet can be broken in halves to provide recommended dosage.

To break URSO Forte scored tablet easily, place the tablet on a flat surface with the scored section on top. Hold the tablet with your thumbs placed close to the scored part of the tablet (groove). Then apply gentle pressure and snap the tablet segments apart (segments breaking incorrectly should not be used). The segments should be washed down unchewed, with water, keeping the segments in the mouth can reveal a bitter taste. Due to the bitter taste, segments should be stored separately from whole tablets. [see How Supplied/Storage and Handling (16)].

3 DOSAGE FORMS AND STRENGTHS

- URSO 250: 250 mg tablet
- URSO Forte: 500 mg scored tablet

4 CONTRAINDICATIONS

Patients with complete biliary obstruction and known hypersensitivity or intolerance to ursodiol or any of the components of the formulation.

5 WARNINGS AND PRECAUTIONS

5.1 Abnormal Liver Function Tests

Liver function tests (γ-GT, alkaline phosphatase, AST, ALT) and bilirubin levels should be monitored every month for three months after start of therapy, and every six months thereafter. This monitoring will allow the early detection of a possible deterioration of the hepatic function. Treatment discontinuation should be considered if the above parameters increase to a level considered clinically significant in patients with stable historical liver function test levels.

Caution has to be exercised to maintain the bile flow of the patients taking ursodiol.

5.2 Enteroliths in Patients with Risk for Intestinal Stenosis or Stasis

There have been rare postmarketing reports of URSO-treated patients who developed enteroliths (bezoars) resulting in obstructive symptoms that required surgical intervention. These patients had medical conditions that predisposed them to intestinal stenosis or stasis (e.g., surgical enteroanastomoses, Crohn's disease). If a patient presents with obstructive gastrointestinal symptoms, hold URSO until a clinical evaluation has been conducted.

6 ADVERSE REACTIONS

6.1 Clinical Studies Experience

Because clinical trials are conducted under widely varying conditions, adverse reaction rates observed in the clinical trials of a drug cannot be directly compared to rates in the clinical trials of another drug and may not reflect the rates observed in clinical practice.

The following table summarizes the adverse reactions observed in two placebo-controlled clinical trials.

ADVERSE REACTIONS | VISIT AT 12 MONTHS |  | VISIT AT 24 MONTHS
 | UDCA n (%) | Placebo n (%) | UDCA n (%) | Placebo n (%)
Diarrhea | --- | --- | 1 (1.32) | ---
Elevated creatinine | --- | --- | 1 (1.32) | ---
Elevated blood glucose | 1 (1.18) | --- | 1 (1.32) | ---
Leukopenia | --- | --- | 2 (2.63) | ---
Peptic ulcer | --- | --- | 1 (1.32) | ---
Skin rash | --- | --- | 2 (2.63) | ---
Thrombocytopenia | --- | --- | 1 (1.32) | ---
Note: Those adverse reactions occurring at the same or higher incidence in the placebo as in the UDCA group have been deleted from this table (this includes diarrhea and thrombocytopenia at 12 months, nausea/vomiting, fever and other toxicity).
UDCA = Ursodeoxycholic acid = Ursodiol

In a randomized, cross-over study in sixty PBC patients, seven patients (11.6%) reported nine adverse reactions: abdominal pain and asthenia (1 patient), nausea (3 patients), dyspepsia (2 patients) and anorexia and esophagitis (1 patient each). One patient on the twice a day regimen (total dose 1,000 mg) withdrew due to nausea. All of these nine adverse reactions except esophagitis were observed with the twice a day regimen at a total daily dose of 1,000 mg or greater. However, an adverse reaction may occur at any dose.

6.2 Postmarketing Experience

The following adverse reactions, presented by system organ class in alphabetical order, have been identified during post approval use of ursodiol. Because these reactions are reported voluntarily from a population of uncertain size, it is not always possible to reliably estimate their frequency or establish a causal relationship to drug exposure.

- Gastrointestinal disorders: abdominal discomfort, abdominal pain, enteroliths (bezoars), constipation, diarrhea, dyspepsia, nausea, vomiting.
- General disorders and administration site conditions: malaise, peripheral edema, pyrexia.
- Hepatobiliary disorders: jaundice (or aggravation of pre-existing jaundice).
- Immune System Disorders: Drug hypersensitivity to include facial edema, urticaria, angioedema and laryngeal edema.
- Abnormal Laboratory Tests: ALT increased, AST increased, blood alkaline phosphatase increased, blood bilirubin increased, γ-GT increased, hepatic enzyme increased, liver function test abnormal, transaminases increased.
- Musculoskeletal and connective tissue disorders: myalgia
- Nervous system disorders: dizziness, headache.
- Respiratory, thoracic and mediastinal disorders: cough.
- Skin and subcutaneous tissue disorder: alopecia, pruritus, rash.

7 DRUG INTERACTIONS

7.1 Bile Acid Sequestering Agents

Bile acid sequestering agents such as cholestyramine and colestipol may interfere with the action of URSO 250 and URSO Forte by reducing its absorption.

7.2 Aluminum-based Antacids

Aluminum-based antacids have been shown to adsorb bile acids in vitro and may be expected to interfere with URSO 250 and URSO Forte in the same manner as the bile acid sequestering agents.

7.3 Drugs Affecting Lipid Metabolism

Estrogens, oral contraceptives, and clofibrate (and perhaps other lipid-lowering drugs) increase hepatic cholesterol secretion and encourage cholesterol gallstone formation and hence may counteract the effectiveness of URSO 250 and URSO Forte.

8 USE IN SPECIFIC POPULATIONS

8.1 Pregnancy

Risk Summary

Available published data on the use of ursodiol in pregnant women derived from randomized controlled trials, observational studies, and case series collected over several decades have not identified a drug-associated risk of major birth defects, miscarriage, or other adverse maternal or fetal outcomes. Most of the reported exposures to ursodiol occurred in the second and third trimester of pregnancy. In animal reproduction studies, ursodiol had no adverse effects on embryo-fetal development when administered at doses greater than human therapeutic doses (see Data).

The estimated background risk of major birth defects and miscarriage for the indicated population is unknown. All pregnancies have a background risk of birth defect, loss, or other adverse outcomes. In the U.S. general population, the estimated background risk of major birth defects and miscarriage in the clinically recognized pregnancies is 2 to 4% and 15 to 20%, respectively.

Data

Animal Data

No adverse effects on embryo-fetal development were observed with oral administration of ursodiol to pregnant rats and rabbits during organogenesis at doses up to 22 and 7 times, respectively, the maximum recommended human dose (based on body surface area).

8.2 Lactation

Risk Summary

Ursodiol is naturally present in human milk. There are no reports of adverse effects of ursodiol on the breastfed child, but the reports are extremely limited. There are no data on the effects of ursodiol on milk production. The developmental and health benefits of breastfeeding should be considered along with the mother’s clinical need for URSO 250 and URSO Forte and any potential adverse effects on the breastfed child from URSO 250 and URSO Forte or from the underlying maternal condition.

8.4 Pediatric Use

The safety and effectiveness of URSO 250 and URSO Forte in pediatric patients have not been established.

10 OVERDOSAGE

There have been no reports of accidental or intentional overdosage with ursodiol. Single oral doses of ursodiol at 10 g/kg in mice and dogs, and 5 g/kg in rats were not lethal. A single oral dose of ursodiol at 1.5 g/kg was lethal in hamsters. Symptoms of acute toxicity were salivation and vomiting in dogs, and ataxia, dyspnea, ptosis, agonal convulsions and coma in hamsters.

11 DESCRIPTION

URSO 250 (ursodiol, 250 mg) is available as a film-coated tablet for oral administration. URSO Forte (ursodiol, 500 mg) is available as a scored film-coated tablet for oral administration.

Ursodiol (ursodeoxycholic acid, UDCA) is a naturally occurring bile acid found in small quantities in normal human bile and in larger quantities in the biles of certain species of bears. It is a bitter-tasting white powder consisting of crystalline particles freely soluble in ethanol and glacial acetic acid, slightly soluble in chloroform, sparingly soluble in ether, and practically insoluble in water. The chemical name of ursodiol is 3α,7ß-dihydroxy-5ß-cholan-24-oic (C24H40O4). Ursodiol has a molecular weight of 392.56. Its structure is shown below.

Inactive ingredients: microcrystalline cellulose, povidone, sodium starch glycolate, magnesium stearate, ethylcellulose, dibutyl sebacate, carnauba wax, hydroxypropyl methylcellulose, PEG 3350, PEG 8000, cetyl alcohol, sodium lauryl sulfate and hydrogen peroxide.

12 CLINICAL PHARMACOLOGY

12.1 Mechanism of Action

Ursodiol, a naturally occurring hydrophilic bile acid, derived from cholesterol, is present as a minor fraction of the total human bile acid pool. Oral administration of ursodiol increases this fraction in a dose related manner, to become the major biliary acid, replacing/displacing toxic concentrations of endogenous hydrophobic bile acids that tend to accumulate in cholestatic liver disease.

In addition to the replacement and displacement of toxic bile acids, other mechanisms of action include cytoprotection of the injured bile duct epithelial cells (cholangiocytes) against toxic effects of bile acids, inhibition of apoptosis of hepatocytes, immunomodulatory effects, and stimulation of bile secretion by hepatocytes and cholangiocytes.

12.2 Pharmacodynamics

Lithocholic acid, when administered chronically to animals, causes cholestatic liver injury that may lead to death from liver failure in certain species unable to form sulfate conjugates. Ursodiol is 7-dehydroxylated more slowly than chenodiol. For equimolar doses of ursodiol and chenodiol, steady state levels of lithocholic acid in biliary bile acids are lower during ursodiol administration than with chenodiol administration. Humans and chimpanzees can sulfate lithocholic acid. Although liver injury has not been associated with ursodiol therapy, a reduced capacity to sulfate may exist in some individuals.

12.3 Pharmacokinetics

Ursodiol (UDCA) is normally present as a minor fraction of the total bile acids in humans (about 5%). Following oral administration, the majority of ursodiol is absorbed by passive diffusion and its absorption is incomplete. Once absorbed, ursodiol undergoes hepatic extraction to the extent of about 50% in the absence of liver disease. As the severity of liver disease increases, the extent of extraction decreases. In the liver, ursodiol is conjugated with glycine or taurine, then secreted into bile. These conjugates of ursodiol are absorbed in the small intestine by passive and active mechanisms. The conjugates can also be deconjugated in the ileum by intestinal enzymes, leading to the formation of free ursodiol that can be reabsorbed and reconjugated in the liver. Nonabsorbed ursodiol passes into the colon where it is mostly 7-dehydroxylated to lithocholic acid. Some ursodiol is epimerized to chenodiol (CDCA) via a 7-oxo intermediate. Chenodiol also undergoes 7-dehydroxylation to form lithocholic acid. These metabolites are poorly soluble and excreted in the feces. A small portion of lithocholic acid is reabsorbed, conjugated in the liver with glycine, or taurine and sulfated at the 3 position. The resulting sulfated lithocholic acid conjugates are excreted in bile and then lost in feces.

In healthy subjects, at least 70% of ursodiol (unconjugated) is bound to plasma protein. No information is available on the binding of conjugated ursodiol to plasma protein in healthy subjects or PBC patients. Its volume of distribution has not been determined, but is expected to be small since the drug is mostly distributed in the bile and small intestine. Ursodiol is excreted primarily in the feces. With treatment, urinary excretion increases, but remains less than 1% except in severe cholestatic liver disease.

During chronic administration of ursodiol, it becomes a major biliary and plasma bile acid. At a chronic dose of 13 to 15 mg/kg/day, ursodiol constitutes 30-50% of biliary and plasma bile acids.

13 NONCLINICAL TOXICOLOGY

13.1 Carcinogenesis, Mutagenesis, Impairment of Fertility

In two 24-month oral carcinogenicity studies in mice, ursodiol at doses up to 1,000 mg/kg/day (3,000 mg/m^2/day) was not tumorigenic. Based on body surface area, for a 50 kg person of average height (1.46 m^2 body surface area), this dose represents 5.4 times the recommended maximum clinical dose of 15 mg/kg/day (555 mg/m^2/day).

In a two-year oral carcinogenicity study in Fischer 344 rats, ursodiol at doses up to 300 mg/kg/day (1,800 mg/m^2/day, 3.2 times the recommended maximum human dose based on body surface area) was not tumorigenic.

In a life-span (126-138 weeks) oral carcinogenicity study, Sprague-Dawley rats were treated with doses of 33 to 300 mg/kg/day, 0.4 to 3.2 times the recommended maximum human dose based on body surface area. Ursodiol produced a significantly (p≤0.5, Fisher's exact test) increased incidence of pheochromocytomas of the adrenal medulla in females of the highest dose group.

In 103-week oral carcinogenicity studies of lithocholic acid, a metabolite of ursodiol, doses up to 250 mg/kg/day in mice and 500 mg/kg/day in rats did not produce any tumors. In a 78-week rat study, intrarectal instillation of lithocholic acid (1 mg/kg/day) for 13 months did not produce colorectal tumors. A tumor-promoting effect was observed when it was administered after a single intrarectal dose of a known carcinogen N-methyl-N'-nitro-N-nitrosoguanidine. On the other hand, in a 32-week rat study, ursodiol at a daily dose of 240 mg/kg (1,440 mg/m^2, 2.6 times the maximum recommended human dose based on body surface area) suppressed the colonic carcinogenic effect of another known carcinogen azoxymethane.

Ursodiol was not genotoxic in the Ames test, the mouse lymphoma cell (L5178Y, TK+/-) forward mutation test, the human lymphocyte sister chromatid exchange test, the mouse spermatogonia chromosome aberration test, the Chinese hamster micronucleus test and the Chinese hamster bone marrow cell chromosome aberration test.

Ursodiol at oral doses of up to 2,700 mg/kg/day (16,200 mg/m^2/day, 29 times the recommended maximum human dose based on body surface area) was found to have no effect on fertility and reproductive performance of male and female rats.

14 CLINICAL STUDIES

14.1 Efficacy of Ursodeoxycholic Acid Administered at 13 to 15 mg/kg/day in 3 or 4 Divided Doses to PBC Patients

A U.S., multicenter, randomized, double-blind, placebo-controlled study was conducted to evaluate the efficacy of ursodeoxycholic acid at a dose of 13 to 15 mg/kg/day, administered in 3 or 4 divided doses in 180 patients with PBC (78% received four times a day dosage). Upon completion of the double-blind portion, all patients entered an open-label active treatment extension phase.

Treatment failure, the main efficacy endpoint measured during this study, was defined as death, need for liver transplantation, histologic progression by two stages or to cirrhosis, development of varices, ascites or encephalopathy, marked worsening of fatigue or pruritus, inability to tolerate the drug, doubling of serum bilirubin and voluntary withdrawal. After two years of double-blind treatment, the incidence of treatment failure was significantly (p<0.01) reduced in the URSO 250 mg group (20 of 86 (23%) as compared to the placebo group (40 of 86 (47%). Time to treatment failure, which excluded doubling of serum bilirubin and voluntary withdrawal, was also significantly (p<0.001) delayed in the URSO 250 treated group (n=86, 803.8±24.9 d vs. 641.1±24.4 d for the placebo group (n=86) on average) regardless of either histologic stage or baseline bilirubin levels (>1.8 or <1.8 mg/dL).

Using a definition of treatment failure, which excluded doubling of serum bilirubin and voluntary withdrawal, time to treatment failure was significantly delayed in the URSO 250 group. In comparison with placebo, treatment with URSO 250 resulted in a significant improvement in the following serum hepatic biochemistries when compared to baseline: total bilirubin, SGOT, alkaline phosphatase and IgM.

14.2 Efficacy of Ursodiol Administered at 14 mg/kg/day as a Once Daily Dose to PBC Patients

A second study conducted in Canada randomized 222 PBC patients to ursodiol, 14 mg/kg/day or placebo, administered as a once daily dose in a double-blind manner during a two-year period. At two years, a statistically significant (p<0.001) difference between the two treatments (n=106 for the URSO 250 group and n=106 for the placebo group), in favor of ursodiol, was demonstrated in the following: reduction in the proportion of patients exhibiting a more than 50% increase in serum bilirubin; median percent decrease in bilirubin (-17.12% for the URSO 250 group vs. +20.00% for the placebo group), transaminases (-40.54% for the URSO 250 group vs. +5.71% for the placebo group) and alkaline phosphatase (-47.61% for the URSO 250 group vs. -5.69% for the placebo group); incidence of treatment failure; and time to treatment failure. The definition of treatment failure included: discontinuing the study for any reason; a total serum bilirubin level greater than or equal to 1.5 mg/dl or increasing to a level equal to or greater than two times the baseline level; and the development of ascites or encephalopathy. Evaluation of patients at 4 years or longer was inadequate due to the high drop-out rate (n=10 withdrew from the URSO 250 group vs. n=15 from the placebo group) and small number of patients. Therefore, death, need for liver transplantation, histological progression by two stages or to cirrhosis, development of varices, ascites or encephalopathy, marked worsening of fatigue or pruritus, inability to tolerate the drug, doubling of serum bilirubin and voluntary withdrawal were not assessed.

14.3 Efficacy of URSO 250 Administered in Twice a Day Versus Four Times a Day Divided Dosing Schedules to PBC Patients

A randomized, two-period crossover study in fifty PBC patients compared efficacy of URSO 250 (ursodiol) in twice a day versus four times a day divided dosing schedules in 50 patients for 6 months in each crossover period. Mean percent changes from baseline in liver test results and Mayo risk score (n=46) and serum enrichment with UDCA (n=34) were not statistically significant with any dosage at any time interval. This study demonstrated that UDCA (13 to 15 mg/kg/day) given twice a day is equally effective to UDCA given four times a day. In addition, URSO 250 was given as a single versus three times a day dosing schedules in 10 patients. Due to the small number of patients in this arm of the study, it was not possible to conduct statistical comparisons between these regimens.

16 HOW SUPPLIED/STORAGE AND HANDLING

16.1 URSO 250

Each URSO 250 elliptical, biconvex, film-coated tablet, white, engraved with "URS785", contains 250 mg of ursodiol. Available in bottles of 100 tablets (NDC 58914-785-10).

16.2 URSO Forte

Each URSO Forte elliptical, biconvex, scored, film-coated tablet, white, engraved with "URS790", contains 500 mg of ursodiol. Available in bottles of 100 tablets (NDC 58914-790-10). Store at 20°C to 25°C (68°F to 77°F). Dispense in a tight container.

Half-tablets (scored URSO Forte 500 mg tablets broken in half) maintain acceptable quality for up to 28 days when stored in the current packaging (bottles) at 20ºC to 25ºC (68ºF to 77ºF). Due to the bitter taste, the halved segments should be stored separately from the whole tablets [see Dosage and Administration (2.2)].

17 PATIENT COUNSELING INFORMATION

Enteroliths in Patients with Risk for Intestinal Stenosis or Stasis

Advise patients or their caretaker(s) to notify their healthcare provider if they experience obstructive gastrointestinal symptoms due to the risk of enteroliths [see Warnings and Precautions (5.2)].

Drug Interactions

Patients should be informed that absorption of URSO 250 and URSO Forte may be reduced if they are taking bile acid sequestering agents, such as cholestyramine and colestipol, aluminum-based antacids, or drugs known to alter the metabolism of cholesterol [see Drug Interactions (7)].

Distributed by:
Allergan USA, Inc.
Madison, NJ 07940
www.allergan.com

URSO 250® and URSO Forte® are registered trademarks of Allergan Sales, LLC.
© 2023 Allergan. All rights reserved.

v4.0USPI785

Principal Display Panel

- Urso 250 Bottle Label
NDC 58914-785-10
100 tablets
Rx only
Urso® 250
(Ursodiol Tablets, USP) 250 mg
Allergan™

Principal Display Panel

- Urso 500 Bottle Label
NDC 58914-790-10
100 tablets
Urso Forte®
(Ursodiol Tablets, USP)
500 mg
Rx only
For the treatment of
Primary Biliary Cirrhosis
Allergan™